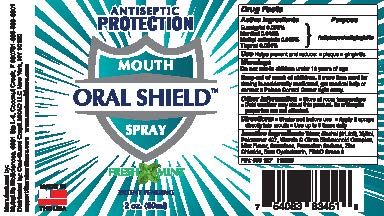 DRUG LABEL: Mouth Oral Shield
NDC: 73761-104 | Form: SPRAY
Manufacturer: Nutralife Biosciences, Inc.
Category: otc | Type: HUMAN OTC DRUG LABEL
Date: 20201207

ACTIVE INGREDIENTS: EUCALYPTOL 0.92 mg/1 mL; MENTHOL 0.42 mg/1 mL; METHYL SALICYLATE 0.6 mg/1 mL; THYMOL 0.64 mg/1 mL
INACTIVE INGREDIENTS: BETADEX; ASCORBIC ACID; ZINC CHLORIDE; POTASSIUM SORBATE; FD&C GREEN NO. 3; WATER; ALCOHOL; XYLITOL; POLOXAMER 407; SUCRALOSE

Mouth Oral Shield Spray

ACTIVE INGREDIENT

Eucalyptol 0.092% Menthol 0.042% Methyl Salicylate 0.060% Thymol 0.064%

PURPOSE

Active ingredients | Purposes
Eucalyptol 0.092% } Menthol 0.042% } Methyl salicylate 0.060% } Thymol 0.064% } | Antiplaque/antigingivitis

Uses

Helps prevent and reduce:

- plaque
- gingivitis

Warnings

Do not use

in children under 12 years of age

Keep out of reach of children.

If more than used for rinsing is accidentally swallowed, get medical help or contact a Poison Control Center right away.

Other information

- Store at room temperature.
- Cold weather may cloud this product. Its antiseptic properties are not affected

Directions

- Shake well before use
- Apply 2 sprays directly into mouth
- Use up to 3 times daily

Inactive ingredients

Water, Alcohol (21.6%), Xylitol, Poloxamer 407, Vitamin C Citrus Bioflavonoid Complex, Mint Flavor, Sucralose, Potassium Sorbate, Zinc Chloride, Beta Cyclodextrin, FD&C Green 3